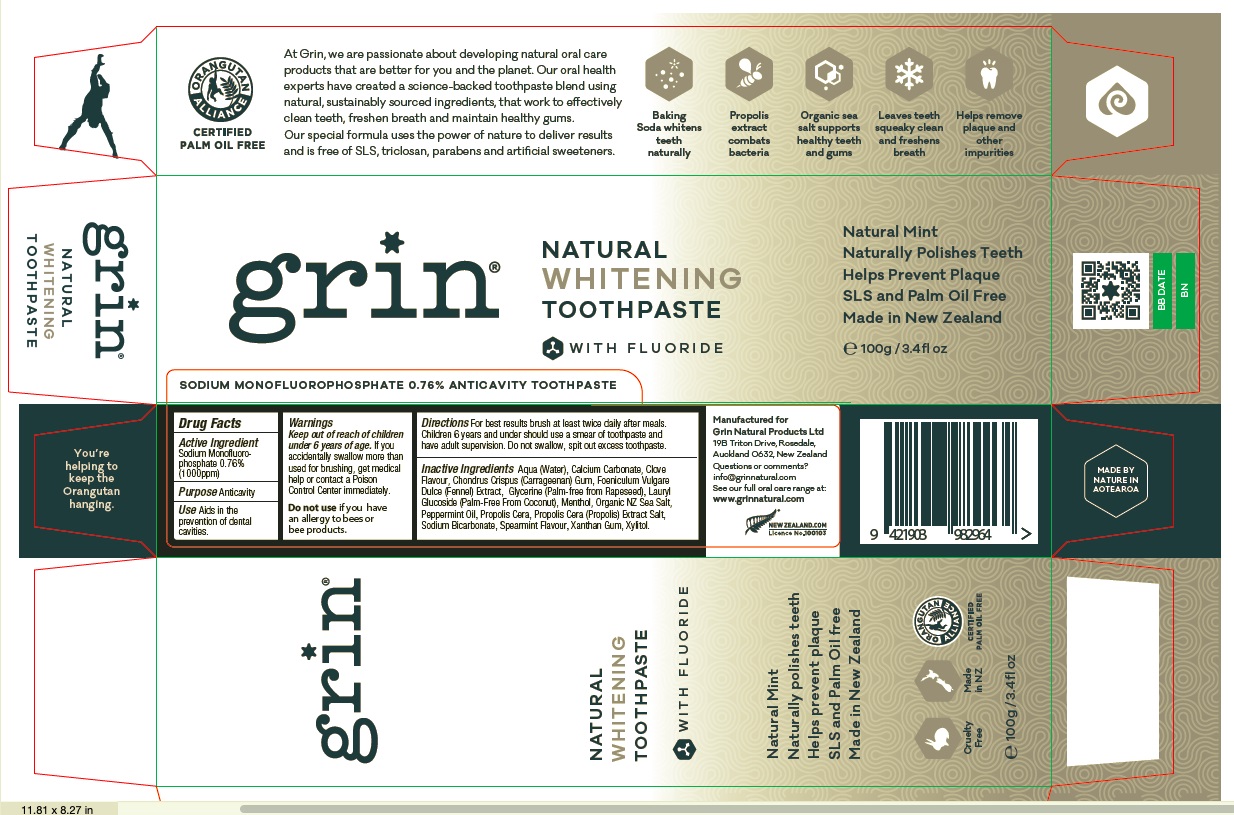 DRUG LABEL: Grin
NDC: 78420-002 | Form: PASTE
Manufacturer: GRIN NATURAL PRODUCTS LIMITED
Category: otc | Type: HUMAN OTC DRUG LABEL
Date: 20200630

ACTIVE INGREDIENTS: SODIUM MONOFLUOROPHOSPHATE 0.76 g/100 g
INACTIVE INGREDIENTS: CALCIUM CARBONATE; GLYCERIN; WATER; XYLITOL; LAURYL GLUCOSIDE; SODIUM BICARBONATE; CHONDRUS CRISPUS CARRAGEENAN; FOENICULUM VULGARE FRUIT; SPEARMINT; CLOVE; MENTHOL; XANTHAN GUM; PEPPERMINT OIL; SEA SALT; PROPOLIS WAX

Active Ingredient

Sodium Monofluorophosphate 0.76% (1000ppm)

Purpose

Anticavity

Use

Aids in the prevention of dental cavities.

Keep out of reach of children under 6 years of age.

Warnings

If you accidentally swallow more than used for brushing, get medical help or contact a Poison Control Center immediately. Do not use if you have an allergy to bees or bee products.

Directions

For best results brush at least twice daily after meals and use in conjunction with Grin dental floss. Children 6 years and under should use a smear of toothpaste and have adult supervision until good habits are established. Do not swallow, spit out excess toothpaste.

Inactive ingredients

Calcium Carbonate, Glycerine (Palm-free from Rapeseed), Aqua (Water), Xylitol, Lauryl Glucoside (Palm-free from Coconut), Sodium Bicarbonate, Chondrus crispus (Carrageenan) Gum, Foeniculum vulgare dulce (Fennel) Extract, Spearmint Flavour, Clove Flavour, Menthol, Xanthan Gum, Peppermint Oil, Organic NZ Sea Salt, Propolis cera (Propolis) Extract